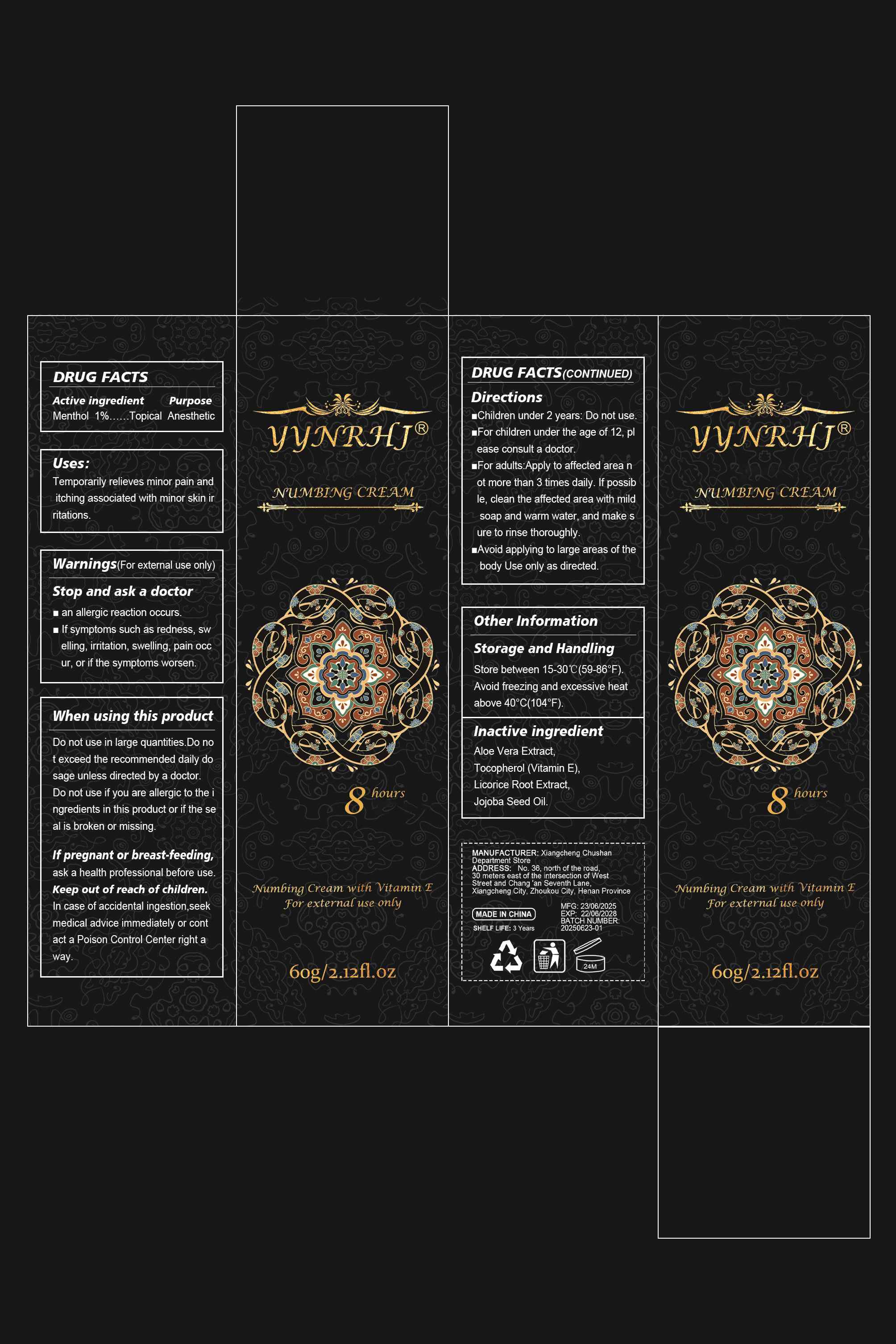 DRUG LABEL: YYNRHJ NUMBING CREAMS
NDC: 85593-005 | Form: CREAM
Manufacturer: Guangzhou ChuanMa International Trading Co.,Ltd.
Category: otc | Type: HUMAN OTC DRUG LABEL
Date: 20250805

ACTIVE INGREDIENTS: MENTHOL 1 g/100 g
INACTIVE INGREDIENTS: ALPHA-TOCOPHEROL; LICORICE; ALOE VERA LEAF; JOJOBA OIL

ACTIVE INGREDIENT

Menthol 1%...Topical Anesthetic

PURPOSE

Temporarily relieves minor pain anditching associated with minor skin irritations.

Stop and ask a doctor
an alergic reaction occurslf symptoms such as redness, swelling, irritation, swelling, pain occur, or if the symptoms worsen.

Do not use in large quantie,.bo not exceed the recommended da dosage unles directed by a docorDo notuse ifyou are alergictothe ingredients in this product or ifthe sea is broken ormising

KEEP OUT OF REACH OF CHILDREN

Keep out of reach of chidrenin case of accidental ingestion,seekmedical advice immediately or contact a Poison Control Center right away.

DOSAGE AND ADMINISTRATION

Children under 2 years: Do not useFor children under the age of 12, please consult a doctorFor adults:Apply to affected area not more than 3 times daily. lf possible, clean the affected area with mildsoap and warm water, and make sure to rinse thoroughly.Avoid applying to large areas of thebody Use only as directed,

Other Information
Storage and HandlingStore between 15-30°C(59-86"F)Avoid freezing and excessive heatabove 40°C(104°F)

INACTIVE INGREDIENT

Aloe Vera Extract,Tocopherol (Vitamin E),Licorice Root Extract.Jojoba Seed Oil.

WARNINGS

Stop and ask a doctor
an allergic reaction occurslf symptoms such as redness, swelling, irritation, swelling, pain occur, or if the symptoms worsen